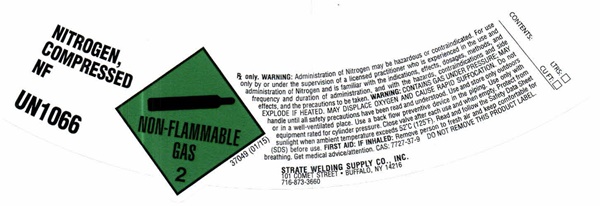 DRUG LABEL: NITROGEN
NDC: 49221-0042 | Form: GAS
Manufacturer: Strate Welding Supply Co., Inc.
Category: prescription | Type: HUMAN PRESCRIPTION DRUG LABEL
Date: 20241028

ACTIVE INGREDIENTS: NITROGEN 99 L/100 L

NITROGEN - 0042

NITROGEN COMPRESSED NF LABEL

NITROGEN COMPRESSED N.F.

UN1066

NON-FLAMMABLE GAS 2

37049 (01/15)

RX only. WARNING: Administration of Nitrogen may be hazardous or contraindicated. For use only by or under the supervision of a licensed practioner who is experienced in the use and administration of Nitrogen and is familiar with the indications, effects, dosages, methods, and frequency and duration of administration, and with the hazards, contraindications and side effects, and the precautions to be taken. WARNING: CONTAINS GAS UNDER PRESSURE; MAY EXPLODE IF HEATED. MAY DISPLACE OXYGEN AND CAUSE REPID SUFFOCATION. Do not handle until all safety precautions have been read and understood. Use and store only outdoors or in a well-ventilated place. Use a back flow preventive device in the piping. Use only with equipment rated for cylinder pressure. Close valve after each use and when empty. protect from sunlight when the ambient temperature exceeds 52°C (125°F). Read and follow the Safety Data Sheet (SDS) before use. FIRST AID: IF INHALED: Remove person to fresh air and keep comfortable for breathing. Get medical advice/attention.

CAS: 7727-37-9 DO NOT REMONE THIS PRODUCT LABEL

STRATE WELDING SUPPLY CO., INC.

101 COMET STREET • BUFFALO, NY 14216

716-873-3660

CONTENTS: LTRS:

CU. FT.